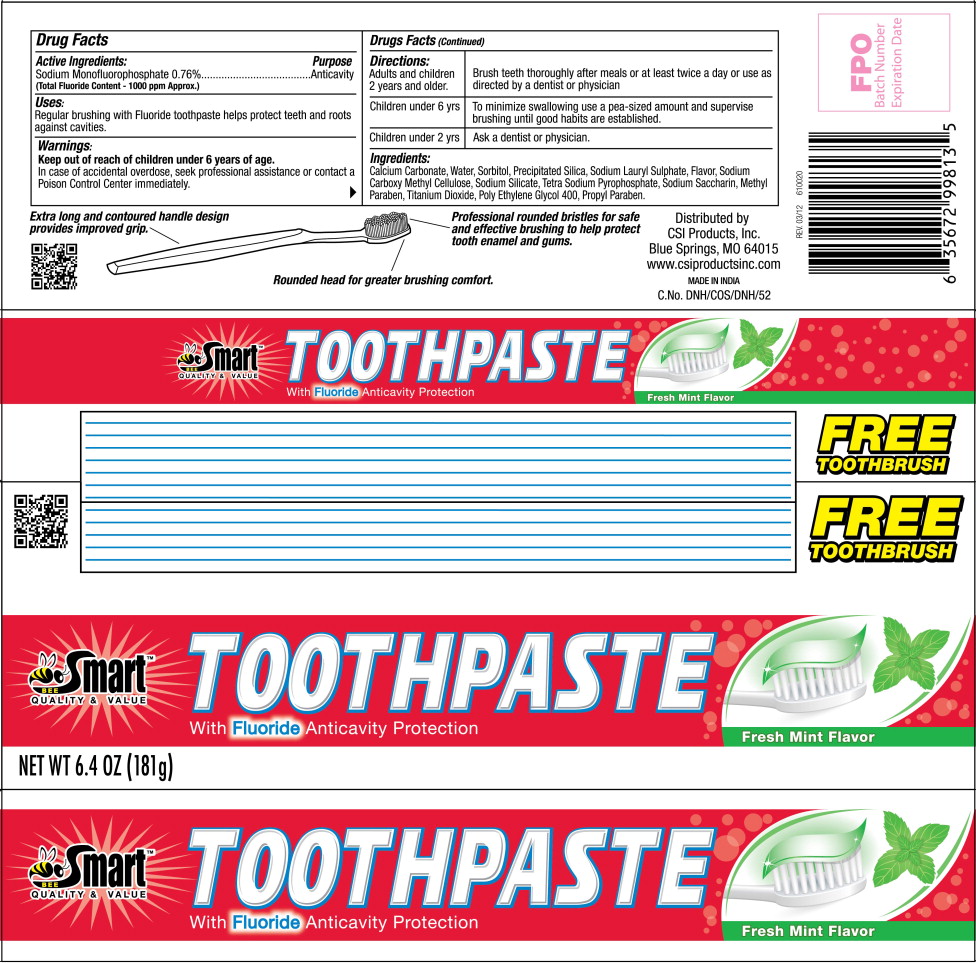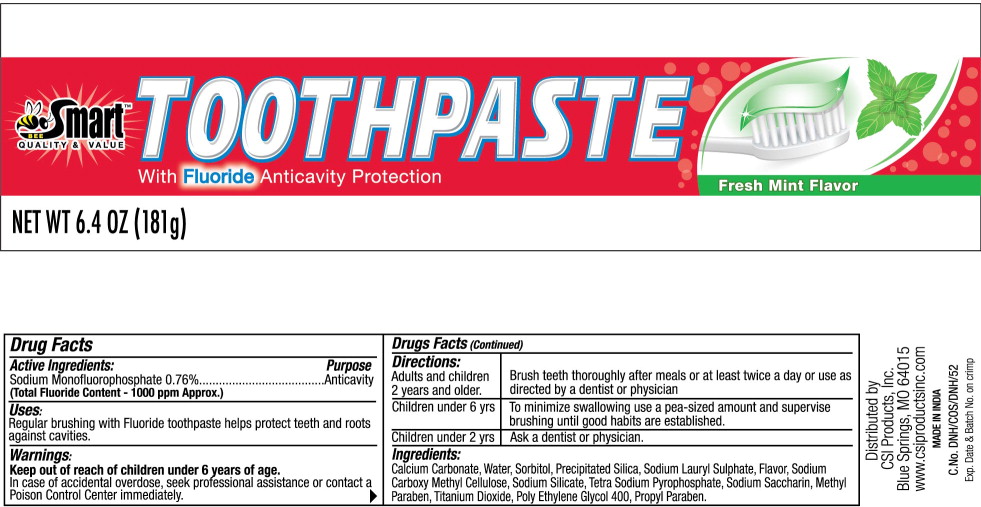 DRUG LABEL: Bee Smart
NDC: 68747-6033 | Form: PASTE, DENTIFRICE
Manufacturer: Dabur India Limited
Category: otc | Type: HUMAN OTC DRUG LABEL
Date: 20080825

ACTIVE INGREDIENTS: SODIUM MONOFLUOROPHOSPHATE 7.6 mg/1 g
INACTIVE INGREDIENTS: CALCIUM CARBONATE; WATER; SORBITOL; SILICON DIOXIDE; SODIUM LAURYL SULFATE; CARBOXYMETHYLCELLULOSE SODIUM; SODIUM PYROPHOSPHATE; SACCHARIN SODIUM; TITANIUM DIOXIDE; METHYLPARABEN; POLYETHYLENE GLYCOL 400; PROPYLPARABEN

Drug Facts

Active Ingredients:

Sodium Monofluorophosphate 0.76%

(Total Fluoride Content – 1000 ppm Approx.)

Purpose

Anticavity

Uses:

Regular brushing with Fluoride toothpaste helps protect teeth and roots against cavities.

Warnings:

Keep out of reach of children under 6 years of age.

In case of accidental overdose, seek professional assistance or contact a Poison Control Center immediately.

DOSAGE AND ADMINISTRATION

Directions: Adult and children 2 years and older. | Brush teeth thoroughly after meals or at least twice a day or use as directed by a dentist or physician.
Children under 6 yrs | To minimize swallowing use a pea-sized amount and supervise brushing until good habits are established.
Children under 2 yrs | Ask a dentist or physician

Ingredients:

Calcium Carbonate, Water, Sorbitol, Precipitated Silica, Sodium Lauryl Sulphate, Flavor, Sodium Carboxy Methyl Cellulose, Sodium Silicate, Tetra Sodium Pyrophosphate, Sodium Saccharin, Methyl Paraben, Titanium Dioxide, Poly Ethylene Glycol 400, Propyl Paraben.

Principal Display Panel – Carton Label

Bee Smart™
QUALITY & VALUE

TOOTHPASTE
With Fluoride Anticavity Protection

Fresh Mint Flavor

NET WT 6.4 OZ (181g)

Principal Display Panel – Tube Label

Bee Smart™
QUALITY & VALUE

TOOTHPASTE
With Fluoride Anticavity Protection

Fresh Mint Flavor

NET WT 6.4 OZ (181g)